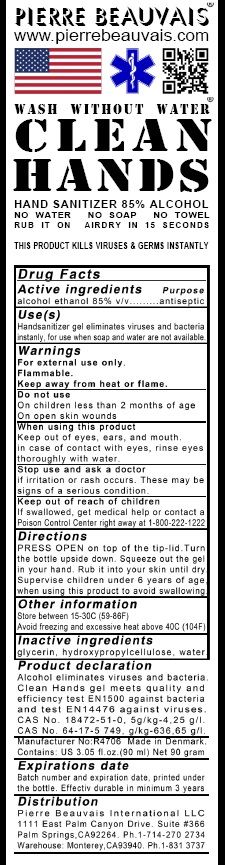 DRUG LABEL: Clean Hands Wash Without Water
NDC: 79908-009 | Form: GEL
Manufacturer: PIERRE BEAUVAIS A/S
Category: otc | Type: HUMAN OTC DRUG LABEL
Date: 20200729

ACTIVE INGREDIENTS: ALCOHOL 85 mL/100 mL
INACTIVE INGREDIENTS: WATER; HYDROXYPROPYL CELLULOSE, UNSPECIFIED; GLYCERIN

Active ingredient

Ethyl alcohol 85%

DOSAGE AND ADMINISTRATION

- PRESS OPEN on top of the tip-lid.
- Turn the bottle upside down.
- Squeeze out the gel in your hand. Rub it into your skin until dry.
- Supervise children under 6 years of age when using this product to avoid swallowing.

Purpose

Antiseptic.

Use

Handsanitizer gel eliminates viruses and bacteria instantly, for use when soap and water not available.

Warnings

For external use only.Flammable.
Keep away from heat or flame.

Do not use

- On children less than 2 months of age.
- On open skin wounds.

When using this product

- Keep out of eyes, ears, and mouth.
- in case of contact with eyes, rinse eyes thoroughly with water.

Stop use and ask a doctor

- if irritation or rash occurs.
- These may be signs of a serious condition.

keep out of reach of children

- If swallowed, get medical help or contact a Poison Control Center right away at 1-800-222-1222.

Inactive Ingredients.

Water,Hydroxypropylcellulose,Glycerin

Other Information

- Store between 15-30C (59-86F)
- Avoid freezing and excessive heat above 40C (104F)